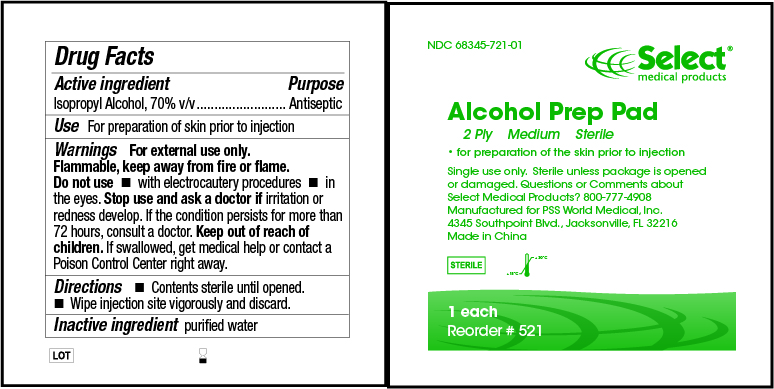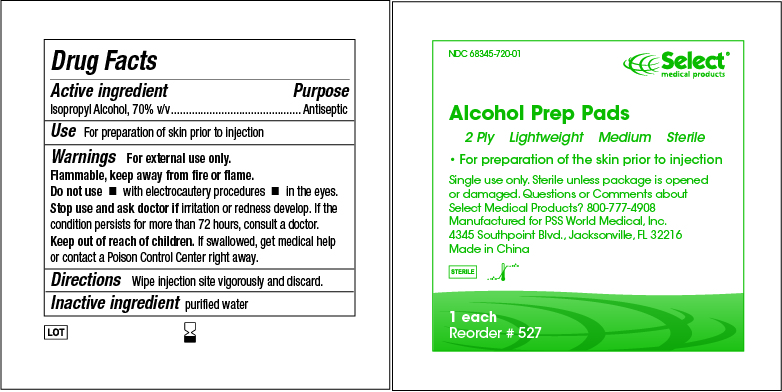 DRUG LABEL: Alcohol Prep Pad
NDC: 68345-721 | Form: SWAB
Manufacturer: PSS World Medical, Inc.
Category: otc | Type: HUMAN OTC DRUG LABEL
Date: 20120905

ACTIVE INGREDIENTS: ISOPROPYL ALCOHOL 70 mL/100 mL
INACTIVE INGREDIENTS: WATER

Alcohol Prep Pad

Active Ingredient

Isopropyl Alcohol, 70% v/v

Purpose

Antiseptic

Use

For preparation of skin prior to injection

Warnings

For external use only.
Flammable, keep away from fire or flame.

Do not use

- with electrocautery procedures
- in the eyes.

Stop use and ask a doctor if

irritation or redness develop. If the condition persists for more than 72 hours, consult a doctor.

Keep out of reach of children. If swallowed, get medical help or contact a Poison Control Center right away.

Directions

Contents sterile until opened.
Wipe injection site vigorously and discard.

Inactive Ingredients

Purified water

Questions

Questions or Comments about Select Medical Products? 800-777-4908
Manufactured for PSS World Medical, Inc.
4345 Southpoint Blvd., Jacksonville, FL 32216
Made in China

Principal Display Panel

68345-721-01

521 ALCOHOL PREP PAD
2 Ply Medium Sterile
For preparation of the skin prior to injection
Single use only.
Sterile unless package is opened or damaged.

Principal Display Panel

68345-720-01

527 ALCOHOL PREP PAD
2 Ply Lightweight Medium Sterile
For preparation of the skin prior to injection
Single use only.
Sterile unless package is opened or damaged.